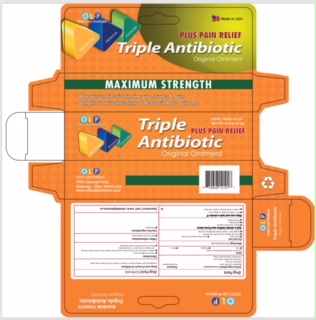 DRUG LABEL: OLP Triple Antibiotic Plus
NDC: 70648-121 | Form: OINTMENT
Manufacturer: Ohio Lab Pharma
Category: otc | Type: HUMAN OTC DRUG LABEL
Date: 20181126

ACTIVE INGREDIENTS: BACITRACIN ZINC 400 [USP'U]/1 g; NEOMYCIN SULFATE 3.5 mg/1 g; POLYMYXIN B SULFATE 5000 [USP'U]/1 g; PRAMOXINE HYDROCHLORIDE 10 mg/1 g
INACTIVE INGREDIENTS: PETROLATUM

Active ingredients

Bacitracin zinc 400 units
Neomycin 3.5 mg
Polymyxin B sulfate 5,000 units

Pramoxine hydrochloride 10 mg

USES

first aid to help prevent infection in minor
• cuts
• scrapes
• burns

Purpose

- first aid antibiotic
- External Analgesic

Warnings

For external use only

Do not use

• if you are allergic to any of the ingredients
• in the eyes
• over large areas of the body
• longer than 1 week unless directed by a doctor

Ask a doctor before use if you have
• deep or puncture wounds
• animal bites
• serious burns

Stop use and ask a doctor if
• the condition persists or gets worse
• a rash or other allergic reaction develops

Keep out of reach of children

If swallowed, get medical help or contact a Poison Control Center right away.

Directions

• clean the affected area
• apply a small amount of this product (an amount equal to the surface area of the tip of a finger) on the area 1 to 3 times daily
• may be covered with a sterile bandage

Other information

Store at room temperature

Inactive ingredient

Petrolatum

Questions

www.ohiolabpharma.us

PACKAGE LABEL

Net Weight 0.33 oz (9.4g0

NDC#70648-121-01